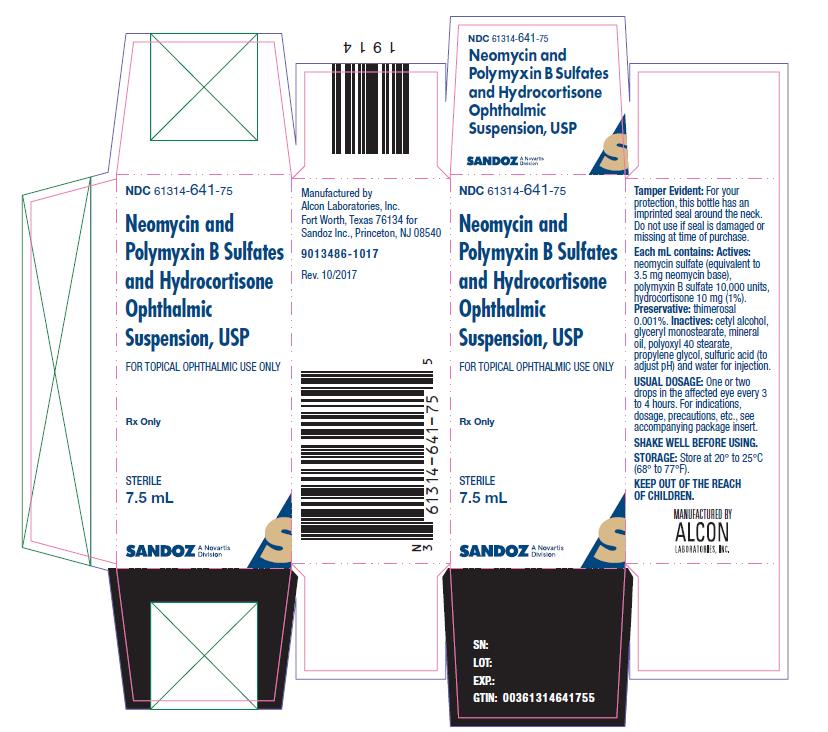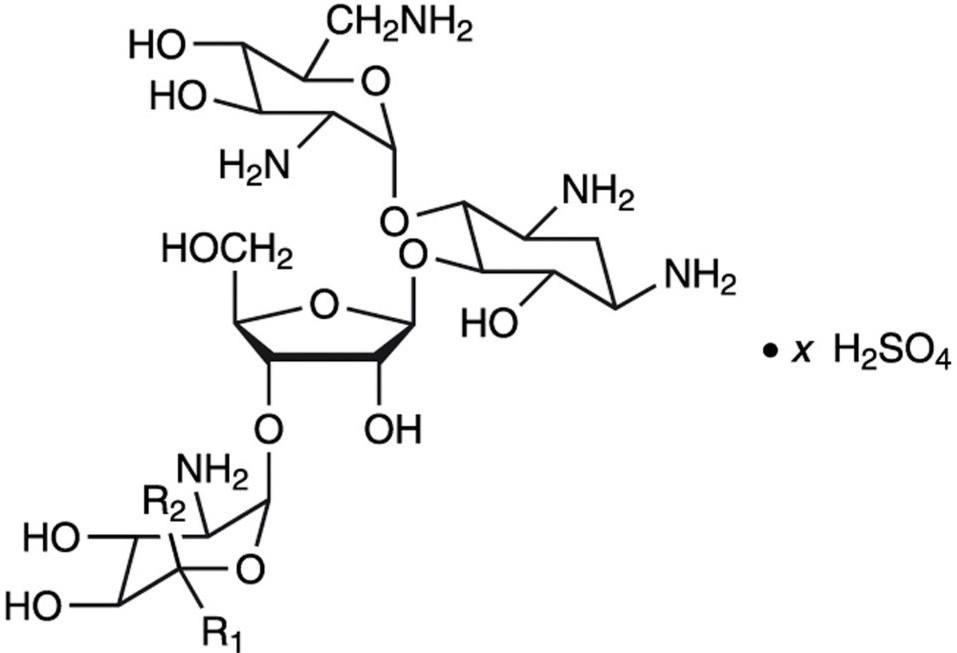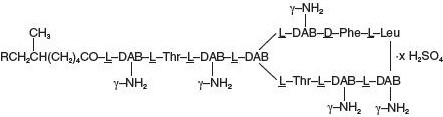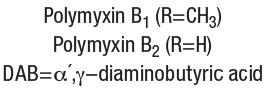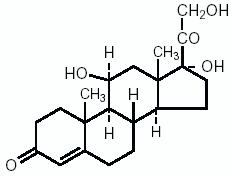 DRUG LABEL: Neomycin and Polymyxin B Sulfates and Hydrocortisone
NDC: 61314-641 | Form: SUSPENSION
Manufacturer: Sandoz Inc
Category: prescription | Type: HUMAN PRESCRIPTION DRUG LABEL
Date: 20210831

ACTIVE INGREDIENTS: NEOMYCIN SULFATE 3.5 mg/1 mL; POLYMYXIN B SULFATE 10000 [USP'U]/1 mL; HYDROCORTISONE 10 mg/1 mL
INACTIVE INGREDIENTS: THIMEROSAL; CETYL ALCOHOL; GLYCERYL MONOSTEARATE; MINERAL OIL; POLYOXYL 40 STEARATE; PROPYLENE GLYCOL; SULFURIC ACID; WATER

NEOMYCIN AND POLYMYXIN B SULFATES AND HYDROCORTISONE OPHTHALMIC SUSPENSION, USP

DESCRIPTION

Neomycin and Polymyxin B Sulfates and Hydrocortisone Ophthalmic Suspension is a sterile antimicrobial and anti-inflammatory suspension for ophthalmic use.

Each mL contains: Actives: neomycin sulfate (equivalent to 3.5 mg neomycin base), polymyxin B sulfate equivalent to 10,000 polymyxin B units, and hydrocortisone 10 mg (1%). Preservative: thimerosal 0.001%. Inactives: cetyl alcohol, glyceryl monostearate, mineral oil, polyoxyl 40 stearate, propylene glycol, sulfuric acid (to adjust pH) and water for injection.

Neomycin sulfate is the sulfate salt of neomycin B and C, which are produced by the growth of Streptomyces fradiae Waksman (Fam. Streptomycetacae). It has a potency equivalent to not less than 600 μg of neomycin standard per mg, calculated on an anhydrous basis. Its structural formula are:

Neomycin B (R1=H, R2=CH2NH2)

Neomycin C (R1=CH2NH2, R2=H)

Polymyxin B sulfate is the sulfate salt of Polymyxin, B1 and B2, which are produced by the growth of Bacillus polymyxa (Prazmowski) Migula (Fam. Bacillaceae). It has a potency of not less than 6,000 polymyxin B units per mg calculated on an anhydrous basis. Its structural formula are:

Hydrocortisone, 11β, 17, 21-trihydroxypregn-4-ene-3, 20 dione, is an anti-inflammatory hormone. Its structural formula is:

CLINICAL PHARMACOLOGY

Corticosteroids suppress the inflammatory response to a variety of agents, and they probably delay or slow healing. Since corticosteroids may inhibit the body's defense mechanism against infection, concomitant antimicrobial drugs may be used when this inhibition is considered to be clinically significant in a particular case.

When a decision to administer both a corticosteroid and antimicrobials is made, the administration of such drugs in combination has the advantage of greater patient compliance and convenience, with the added assurance that the appropriate dosage of all drugs is administered. When each type of drug is in the same formulation, compatibility of ingredients is assured and the correct volume of drug is delivered and retained.

The relative potency of corticosteroids depends on the molecular structure, concentration, and release from the vehicle.

Microbiology

The anti-infective components in Neomycin and Polymyxin B Sulfates and Hydrocortisone Ophthalmic Suspension are included to provide action against specific organisms susceptible to it. Neomycin sulfate and polymyxin B sulfate are active in vitro against susceptible strains of the following microorganisms: Staphylococcus aureus, Escherichia coli, Haemophilus influenzae, Klebsiella/Enterobacter species, Neisseria species, and Pseudomonas aeruginosa. The product does not provide adequate coverage against Serratia marcescens and streptococci, including Streptococcus pneumoniae [see Indications and Usage].

INDICATIONS AND USAGE

Neomycin and Polymyxin B Sulfates and Hydrocortisone Ophthalmic Suspension is indicated for steroid-responsive inflammatory ocular conditions for which a corticosteroid is indicated and where bacterial infection or a risk of bacterial ocular infection exists.

Ocular corticosteroids are indicated in inflammatory conditions of the palpebral and bulbar conjunctiva, cornea and anterior segment of the globe where the inherent risk of corticosteroid use in certain infective conjunctivitides is accepted to obtain a diminution in edema and inflammation. They are also indicated in chronic anterior uveitis and corneal injury from chemical, radiation, or thermal burns, or penetration of foreign bodies.

The use of a combination drug with an anti-infective component is indicated where the risk of infection is high or where there is an expectation that potentially dangerous numbers of bacteria will be present in the eye [see Clinical Pharmacology: Microbiology].

The particular anti-infective drugs in this product are active against the following common bacterial eye pathogens: Staphylococcus aureus, Escherichia coli, Haemophilus influenzae, Klebsiella/Enterobacter species, Neisseria species, and Pseudomonas aeruginosa.

The product does not provide adequate coverage against Serratia marcescens and streptococci, including Streptococcus pneumoniae.

CONTRAINDICATIONS

Neomycin and Polymyxin B Sulfates and Hydrocortisone Ophthalmic Suspension is contraindicated in most viral diseases of the cornea and conjunctiva including: epithelial herpes simplex keratitis (dendritic keratitis), vaccinia, and varicella, and also in mycobacterial infection of the eye and fungal diseases of ocular structures.

Neomycin and Polymyxin B Sulfates and Hydrocortisone Ophthalmic Suspension is also contraindicated in individuals who have shown hypersensitivity to any of its components. Hypersensitivity to the antibiotic component occurs at a higher rate than for other components.

WARNINGS

NOT FOR INJECTION INTO THE EYE. Neomycin and Polymyxin B Sulfates and Hydrocortisone Ophthalmic Suspension should never be directly introduced into the anterior chamber of the eye.

Prolonged use of corticosteroids may result in ocular hypertension and/or glaucoma, with damage to the optic nerve, defects in visual acuity and fields of vision, and posterior subcapsular cataract formation.

Prolonged use may suppress the host response and thus increase the hazard of secondary ocular infections. In those diseases causing thinning of the cornea or sclera, perforations have been known to occur with the use of topical corticosteroids. In acute purulent conditions of the eye, corticosteroids may mask infection or enhance existing infection.

If these products are used for 10 days or longer, intraocular pressure should be routinely monitored even though it may be difficult in uncooperative patients. Corticosteroids should be used with caution in the presence of glaucoma.

The use of corticosteroids after cataract surgery may delay healing and increase the incidence of filtering blebs. Use of ocular corticosteroids may prolong the course and may exacerbate the severity of many viral infections of the eye (including herpes simplex). Employment of corticosteroid medication in the treatment of herpes simplex requires great caution.

Topical antibiotics, particularly, neomycin sulfate, may cause cutaneous sensitization. A precise incidence of hypersensitivity reactions (primarily skin rash) due to topical antibiotics is not known. The manifestations of sensitization to topical antibiotics are usually itching, reddening, and edema of the conjunctiva and eyelid. A sensitization reaction may manifest simply as a failure to heal. During long-term use of topical antibiotic products, periodic examination for such signs is advisable, and the patient should be told to discontinue the product if they are observed. Symptoms usually subside quickly on withdrawing the medication. Application of products containing these ingredients should be avoided for the patient thereafter [see Precautions: General].

PRECAUTIONS

General

The initial prescription and renewal of the medication order beyond 20 mL should be made by a physician only after examination of the patient with the aid of magnification, such as slit lamp biomicroscopy and, where appropriate, fluorescein staining. If signs and symptoms fail to improve after 2 days, the patient should be re-evaluated.

The possibility of fungal infections of the cornea should be considered after prolonged corticosteroid dosing. Fungal cultures should be taken when appropriate.

If this product is used for 10 days or longer, intraocular pressure should be monitored [see Warnings].

There have been reports of bacterial keratitis associated with the use of topical ophthalmic products in multiple-dose containers which have been inadvertently contaminated by patients, most of whom had a concurrent corneal disease or a disruption of the ocular epithelial surface [see Precautions: Information for Patients].

Allergic cross-reactions may occur which could prevent the use of any or all of the following antibiotics for the treatment of future infections: kanamycin, paromomycin, streptomycin, and possibly gentamicin.

Information for Patients

Patients should be instructed to avoid allowing the tip of the dispensing container to contact the eye, eyelid, fingers, or any other surface. The use of this product by more than one person may spread infection.

Patients should also be instructed that ocular products, if handled improperly, can become contaminated by common bacteria known to cause ocular infections. Serious damage to the eye and subsequent loss of vision may result from using contaminated products [see Precautions: General].

If the condition persists or gets worse, or if a rash or allergic reaction develops, the patient should be advised to stop use and consult a physician. Do not use this product if you are allergic to any of the listed ingredients.

Keep tightly closed when not in use. Keep out of reach of children.

Carcinogenesis, Mutagenesis, Impairment of Fertility

Long-term studies in animals to evaluate carcinogenic or mutagenic potential have not been conducted with polymyxin B sulfate. Treatment of cultured human lymphocytes in vitro with neomycin increased the frequency of chromosome aberrations at the highest concentrations (80 ug/mL) tested; however, the effects of neomycin on carcinogenesis and mutagenesis in humans are unknown.

Long-term studies in animals (rats, rabbits, mice) showed no evidence of carcinogenicity or mutagenicity attributable to oral administration of corticosteroids. Long-term animal studies have not been performed to evaluate the carcinogenic potential of topical corticosteroids. Studies to determine mutagenicity with hydrocortisone have revealed negative results. Use of corticosteroid medication in the treatment of herpes simplex requires great caution. Polymyxin B has been reported to impair the motility of equine sperm, but its effects on male or female fertility are unknown. Long-term animal studies have not been performed to evaluate the effect on fertility of topical corticosteroids.

Pregnancy

Teratogenic Effects

Pregnancy Category C. Corticosteroids have been found to be teratogenic in rabbits when applied topically at concentrations of 0.5% on days 6 -18 of gestation and in mice when applied topically at a concentration of 15% on days 10 -13 of gestation. There are no adequate and well-controlled studies in pregnant women. Neomycin and Polymyxin B Sulfates and Hydrocortisone Ophthalmic Suspension should be used during pregnancy only if the potential benefit justifies the potential risk to the fetus.

Nursing Mothers

It is not known whether topical administration of corticosteroids could result in sufficient systemic absorption to produce detectable quantities in human milk. Systemically administered corticosteroids appear in human milk and could suppress growth, interfere with endogenous corticosteroid production, or cause other untoward effects. Because of the potential for serious adverse reactions in nursing infants from Neomycin and Polymyxin B Sulfates and Hydrocortisone Ophthalmic Suspension, a decision should be made whether to discontinue nursing or to discontinue the drug, taking into account the importance of the drug to the mother.

Pediatric Use

Safety and effectiveness in pediatric patients have not been established.

Geriatric Use

No overall differences in safety or effectiveness have been observed between elderly and younger patients.

ADVERSE REACTIONS

Adverse reactions have occurred with corticosteroid/anti-infective combination drugs which can be attributed to the corticosteroid component, the anti-infective component, or the combination. The exact incidence is not known.

Reactions occurring most often from the presence of the anti-infective ingredient are allergic sensitization reactions including itching, swelling, and conjunctival erythema [see Warnings]. More serious hypersensitivity reactions, including anaphylaxis, have been reported rarely.

The reactions due to the corticosteroid component in decreasing order of frequency are: elevation of intraocular pressure (IOP) with possible development of glaucoma, and infrequent optic nerve damage; posterior subcapsular cataract formation; and delayed wound healing.

Secondary Infection

The development of secondary infection has occurred after use of combinations containing corticosteroids and antimicrobials. Fungal and viral infections of the cornea are particularly prone to develop coincidentally with long-term applications of a corticosteroid. The possibility of fungal invasion must be considered in any persistent corneal ulceration where corticosteroid treatment has been used.

Local irritation on instillation has also been reported.

To report SUSPECTED ADVERSE REACTIONS, contact Sandoz Inc. at 1-800-525-8747 or FDA at 1-800-FDA-1088 or www.fda.gov/medwatch.

DOSAGE AND ADMINISTRATION

One or two drops in the affected eye every 3 or 4 hours, depending on the severity of the condition. The suspension may be used more frequently if necessary.

Not more than 20 mL should be prescribed initially and the prescription should not be refilled without further evaluation as outlined in PRECAUTIONS above.

HOW SUPPLIED

Neomycin and Polymyxin B Sulfates and Hydrocortisone Ophthalmic Suspension is available in a bottle containing 7.5 mL. NDC 61314-641-75

SHAKE WELL BEFORE USING.

Store at 20° to 25°C (68° to 77°F).

Manufactured by

Alcon Laboratories, Inc.

Fort Worth, Texas 76134 for

Sandoz Inc.

Princeton, NJ 08540

Rev. August 2021

300049861-0821

PRINCIPAL DISPLAY PANEL

NDC 61314-641-75

Neomycin and

Polymyxin B Sulfates

and Hydrocortisone

Ophthalmic

Suspension, USP

FOR TOPICAL OPHTHALMIC USE ONLY

Rx Only

STERILE

7.5 mL

SANDOZ